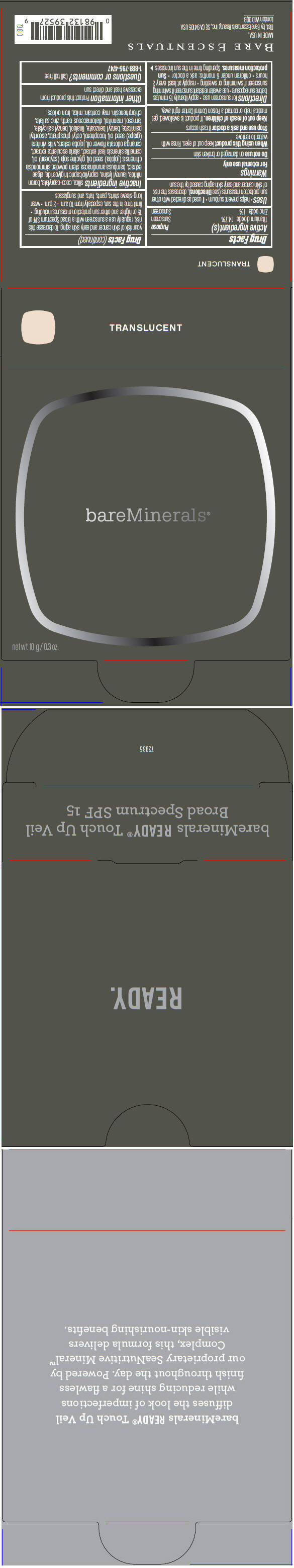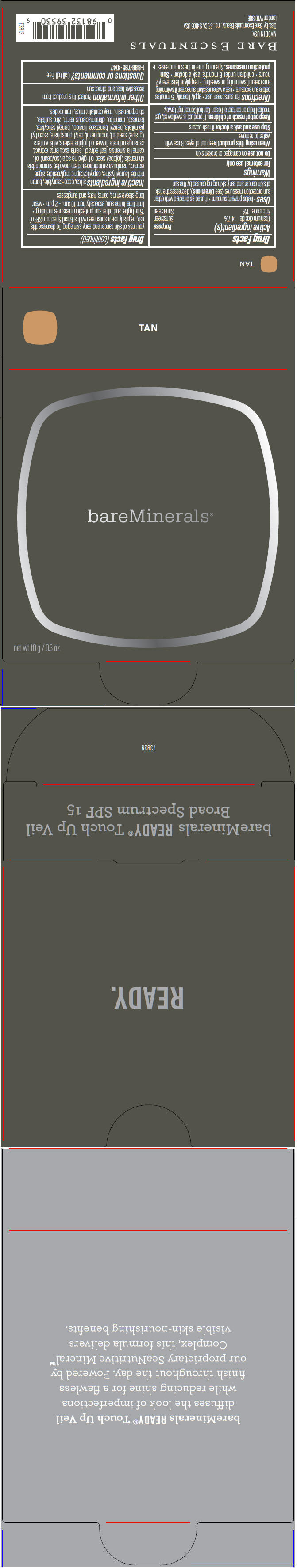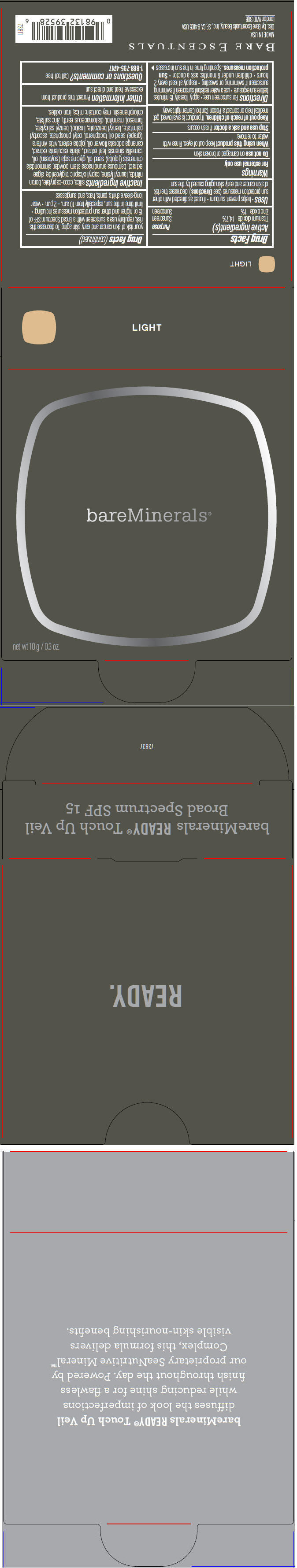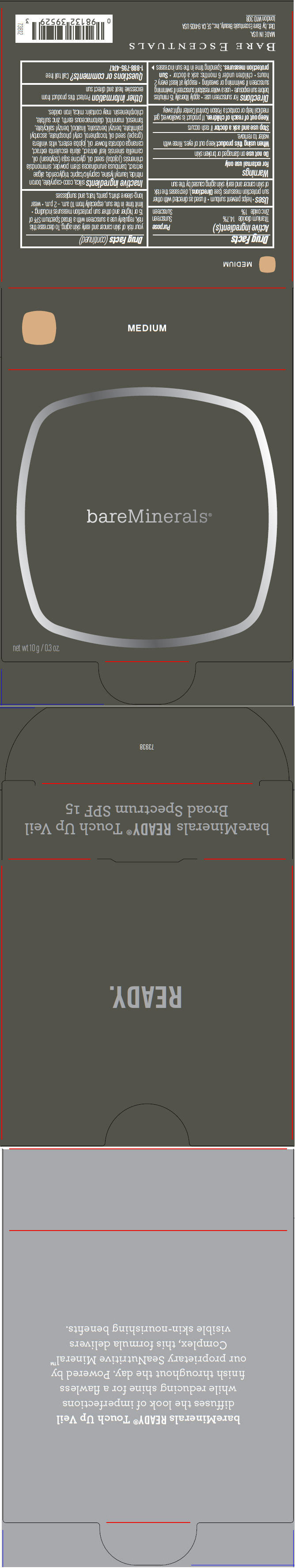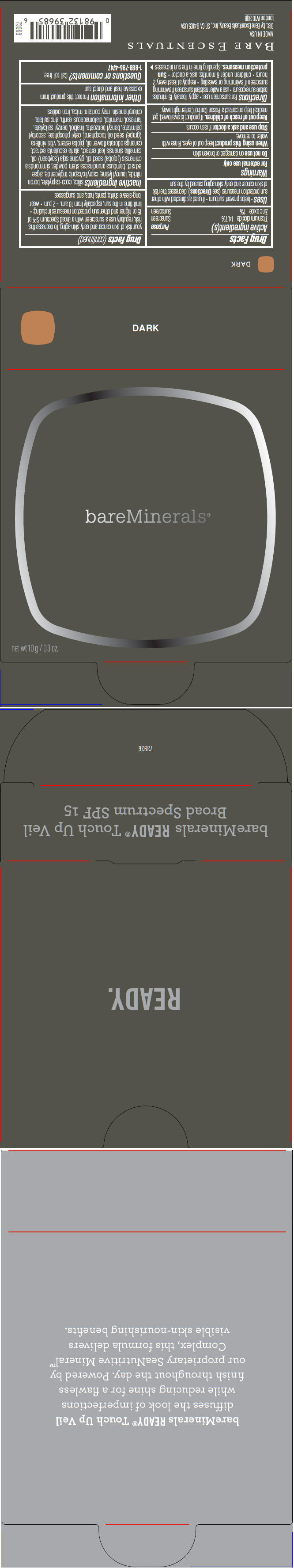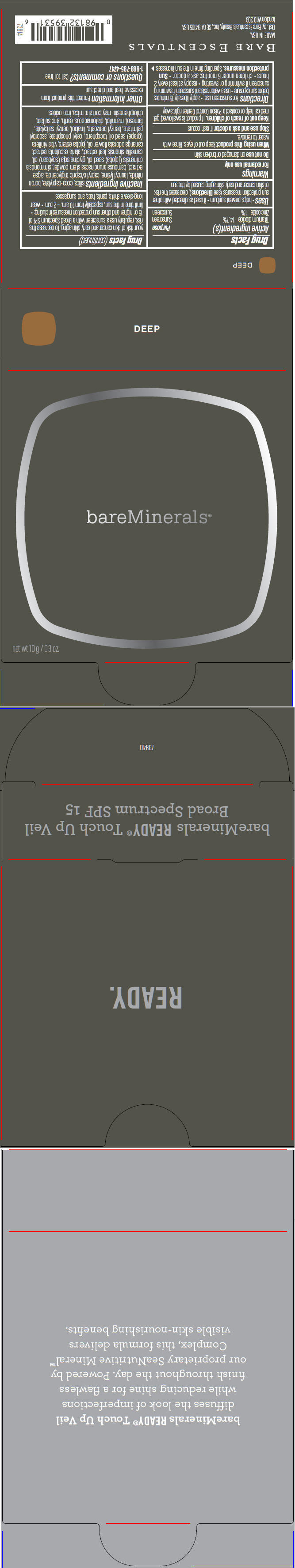 DRUG LABEL: bareMinerals READY Touch Up Veil Broad Spectrum SPF 15
NDC: 98132-300 | Form: POWDER
Manufacturer: Bare Escentuals Beauty Inc.
Category: otc | Type: HUMAN OTC DRUG LABEL
Date: 20181218

ACTIVE INGREDIENTS: TITANIUM DIOXIDE 1470 mg/10 g; ZINC OXIDE 100 mg/10 g
INACTIVE INGREDIENTS: SILICON DIOXIDE; COCO-CAPRYLATE; BORON NITRIDE; LAUROYL LYSINE; MEDIUM-CHAIN TRIGLYCERIDES; BAMBUSA BAMBOS STEM; JOJOBA OIL; SOYBEAN OIL; GREEN TEA LEAF; ALARIA ESCULENTA; CANANGA OIL; GRAPE SEED OIL; TOCOPHEROL; CETYL PHOSPHATE; ASCORBYL PALMITATE; BENZYL BENZOATE; LINALOOL, (+/-)-; BENZYL SALICYLATE; FARNESOL; MANNITOL; DIATOMACEOUS EARTH; ZINC SULFATE, UNSPECIFIED FORM; CHLORPHENESIN; MICA; FERRIC OXIDE RED

bareMinerals® READY® Touch Up Veil Broad Spectrum SPF 15

Drug Facts

Active ingredient(s)

Titanium dioxide 14.7%
Zinc oxide 1%

Purpose

Sunscreen

Uses

- helps prevent sunburn
- if used as directed with other sun protection measures (see Directions), decreases the risk of skin cancer and early skin aging caused by the sun

Warnings

For external use only

Do not use on damaged or broken skin

When using this product keep out of eyes. Rinse with water to remove.

Stop use and ask a doctor if rash occurs

Keep out of reach of children. If product is swallowed, get medical help or contact a Poison Control Center right away.

Directions

For sunscreen use:

- apply liberally 15 minutes before sun exposure
- use a water resistant sunscreen if swimming or sweating
- reapply at least every 2 hours
- Sun Protection Measures. Spending time in the sun increases your risk of skin cancer and early skin aging. To decrease this risk, regularly use a sunscreen with a broad spectrum SPF of 15 or higher and other sun protection measures including:
  - limit time in the sun, especially from 10 a.m. – 2 p.m.
  - wear long-sleeve shirts, pants, hats, and sunglasses
- children under 6 months: Ask a doctor

Inactive ingredients

silica, coco-caprylate, boron nitride, lauroyl lysine, caprylic/capric triglyceride, algae extract, bambusa arundinacea stem powder, simmondsia chinensis (jojoba) seed oil, glycine soja (soybean) oil, camellia sinensis leaf extract, alaria esculenta extract, cananga odorata flower oil, jojoba esters, vitis vinifera (grape) seed oil, tocopherol, cetyl phosphate, ascorbyl palmitate, benzyl benzoate, linalool, benzyl salicylate, farnesol, mannitol, diatomaceous earth, zinc sulfate, chlorphenesin. may contain: mica, iron oxides.

Other information

- protect this product from excessive heat and direct sun.

Questions or comments?

Call toll free 1-888-795-4747

Dist. by Bare Escentuals Beauty, Inc., SF, CA 94105 USA

PRINCIPAL DISPLAY PANEL - 10 g Tray Carton - Translucent

bareMinerals®

net wt 10 g / 0.3 oz.

PRINCIPAL DISPLAY PANEL - 10 g Tray Carton - Tan

bareMinerals®

net wt 10 g / 0.3 oz.

PRINCIPAL DISPLAY PANEL - 10 g Tray Carton - Light

bareMinerals®

net wt 10 g / 0.3 oz.

PRINCIPAL DISPLAY PANEL - 10 g Tray Carton - Medium

bareMinerals®

net wt 10 g / 0.3 oz.

PRINCIPAL DISPLAY PANEL - 10 g Tray Carton - Dark

bareMinerals®

net wt 10 g / 0.3 oz.

PRINCIPAL DISPLAY PANEL - 10 g Tray Carton - Deep

bareMinerals®

net wt 10 g / 0.3 oz.